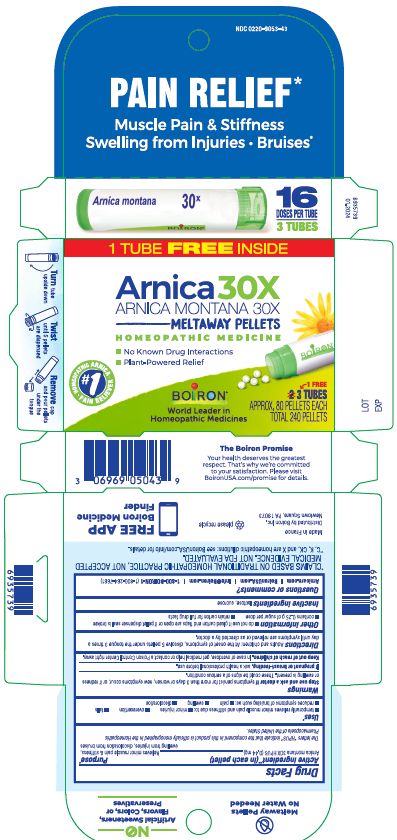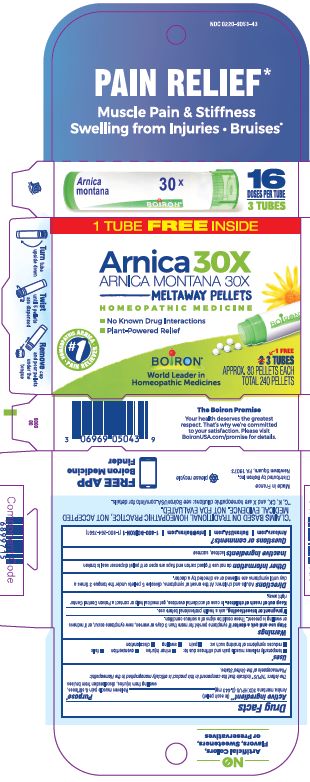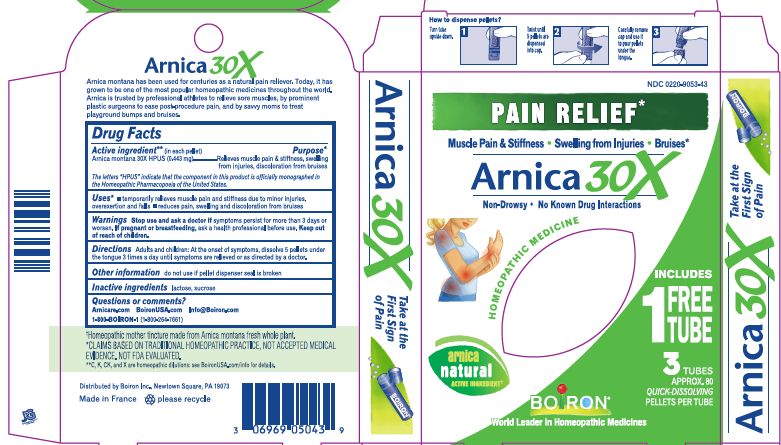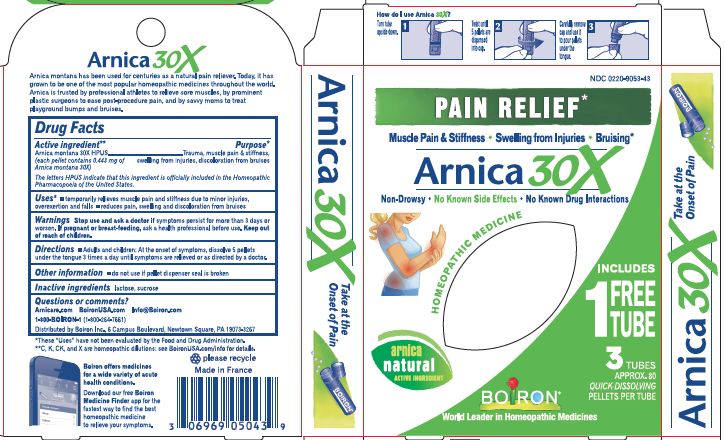 DRUG LABEL: Arnica montana 30X Bonus Pack
NDC: 0220-9053 | Form: PELLET
Manufacturer: Boiron
Category: homeopathic | Type: HUMAN OTC DRUG LABEL
Date: 20240403

ACTIVE INGREDIENTS: ARNICA MONTANA 30 [hp_X]/1 1
INACTIVE INGREDIENTS: LACTOSE, UNSPECIFIED FORM; SUCROSE

Arnica montana 30X Bonus Pack

Active ingredient** (in each pellet)

Arnica montana 30X HPUS (0.44 mg)

The letter "HPUS" indicate that the component in this product is officially monographed in the Homeopathic Pharmacopoeia of the United States.

Purpose*

Relieves minor muscle pain & stiffness, swelling from injuries, discoloration and bruises

Uses*

temporarily relieves minor muscle pain and stiffness due to:

- minor injuries
- overexertion
- falls

reduces symptoms of bruising such as:

- pain
- swelling
- discoloration

Stop use and ask a doctor if symptoms persist for more than 3 days or worsen, new symptoms occur, or if redness or swelling is present. These could be signs of a serious condition.

PREGNANCY OR BREAST FEEDING

If pregnant or breast-feeding, ask a health professional before use.

Keep out of reach of children. In case of overdose, get medical help or contact a Poison Control Center right away.

DOSAGE AND ADMINISTRATION

Directions Adults and children: At the onset of symptoms, dissolve 5 pellets under the tongue 3 times a day until symptoms are relieved or as directed by a doctor.

INACTIVE INGREDIENT

lactose, sucrose

do not use if glued carton end flaps are open or if pellet dispenser seal is broken

How to dispense pellets? Turn tube upside down. Twist until 5 pellets are dispensed Remove cap and pour pellets under the tongue

3 Tubes

Approx. 80 pellets each

Total 240 pellets

16 Doses per tube

Pain relief*

Muscle Pain & Stiffness Swelling from injuries Bruises*

No Know Drug Interactions

Plant-Powered Relief

*CLAIMS BASED ON TRADITIONAL HOMEOPATHIC PRACTICE NOT ACCEPTED MEDICAL EVIDENCE. NOT FDA EVALUATED.
*C,K,CK, and X are homeopathic dilutions: see BoironUSA.com/info for details.

QUESTIONS

Arnicare.com

BoironUSA.com

Info@Boiron.com

1-800-BOIRON-1 (1-800-264-7661)

Distributed by Boiron, Inc.

Newtown Square, PA 19073

Made in France